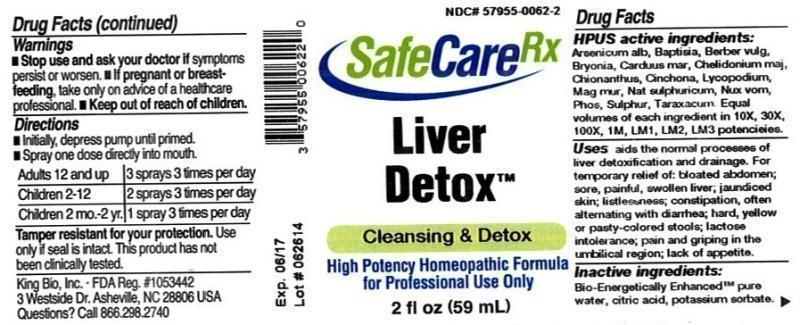 DRUG LABEL: Liver Detox
NDC: 57955-0062 | Form: LIQUID
Manufacturer: King Bio Inc.
Category: homeopathic | Type: HUMAN OTC DRUG LABEL
Date: 20150223

ACTIVE INGREDIENTS: ARSENIC TRIOXIDE 10 [hp_X]/59 mL; BAPTISIA TINCTORIA ROOT 10 [hp_X]/59 mL; BERBERIS VULGARIS ROOT BARK 10 [hp_X]/59 mL; BRYONIA ALBA ROOT 10 [hp_X]/59 mL; MILK THISTLE 10 [hp_X]/59 mL; CHELIDONIUM MAJUS 10 [hp_X]/59 mL; CHIONANTHUS VIRGINICUS BARK 10 [hp_X]/59 mL; CINCHONA OFFICINALIS BARK 10 [hp_X]/59 mL; LYCOPODIUM CLAVATUM SPORE 10 [hp_X]/59 mL; MAGNESIUM CHLORIDE 10 [hp_X]/59 mL; SODIUM SULFATE 10 [hp_X]/59 mL; STRYCHNOS NUX-VOMICA SEED 10 [hp_X]/59 mL; PHOSPHORUS 10 [hp_X]/59 mL; SULFUR 10 [hp_X]/59 mL; TARAXACUM OFFICINALE 10 [hp_X]/59 mL
INACTIVE INGREDIENTS: WATER; ANHYDROUS CITRIC ACID; POTASSIUM SORBATE

Liver Detox™

ACTIVE INGREDIENT

Drug Facts__________________________________________________________________________________________________________

HPUS active ingredients: Arsenicum album, Baptisia tinctoria, Berberis vulgaris, Bryonia, Carduus marianus, Chelidonium majus, Chionanthus virginica, Cinchona officinalis, Lycopodium clavatum, Magnesia muriatica, Natrum sulphuricum, Nux vomica, Phosphorus, Sulphur, Taraxacum officinale. Equal volumes of each ingredient in 10X, 30X, 100X, 1M, LM1, LM2, LM3 potencies.

INDICATIONS AND USAGE

Uses aids the normal processes of liver detoxification and drainage. For temporary relief of: bloated abdomen; sore, painful, swollen liver; jaundiced skin; listlessness; constipation, often alternating with diarrhea; hard, yellow or pasty-colored stools; lactose intolerance; pain and griping in the umbilical region; lack of appetite.

Inactive Ingredients:

Bio-Energetically Enhanced™ pure water, citric acid and potassium sorbate.

Warnings

- Stop use and ask your doctor if symptoms persist or worsen.
- If pregnant or breast-feeding, take only on advice of a healthcare professional.

- Keep out of reach of children.

Directions

- Initially, depress pump until primed.
- Spray one dose directly into mouth.
- Adults 12 and up: 3 sprays 3 times per day
- Children 2-12: 2 sprays 3 times per day
- Children 2 mo.-2 yr.: 1 spray 3 times per day

OTHER SAFETY INFORMATION

Tamper resistant for your protection. Use only if safety seal is intact. This product has not been clinically tested.

PURPOSE

Uses aids the normal processes of liver detoxification and drainage. For temporary relief of:

- bloated abdomen
- sore, painful, swollen liver
- jaundiced skin
- listlessness; constipation
- often alternating with diarrhea; hard, yellow or pasty-colored stools
- lactose intolerance
- pain and griping in the umbilical region
- lack of appetite